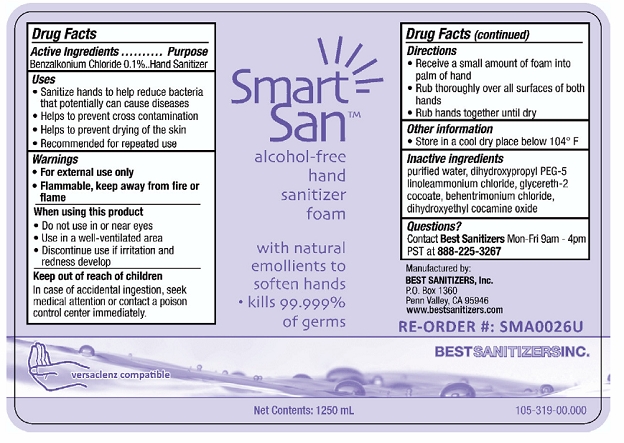 DRUG LABEL: Smart San Alcohol Free Hand Sanitizer Foam
NDC: 59900-118 | Form: LIQUID
Manufacturer: Best Sanitizers, Inc
Category: otc | Type: HUMAN OTC DRUG LABEL
Date: 20241205

ACTIVE INGREDIENTS: BENZALKONIUM CHLORIDE 1 g/1000 mL
INACTIVE INGREDIENTS: GLYCERETH-2 COCOATE; WATER; DIHYDROXYPROPYL PEG-5 LINOLEAMMONIUM CHLORIDE; BEHENTRIMONIUM CHLORIDE; DIHYDROXYETHYL COCAMINE OXIDE

Smart San Alcohol Free Hand Sanitizer Foam 59900-118

Active Ingredient

Benzalkonium Chloride 0.1%

Purpose

Hand Sanitizer

Uses

- Sanitize Hands to help reduce bacteria that potentially can causes disease
- Helps to prevent cross contamination
- Helps to prevent drying of the skin
- Recommended for repeated use

Warnings

- For external use only
- Flammable, keep away from fire or flame

When Using this product

- Do not use in or near eyes
- Use in a well-ventilated area
- Discontinue use if irritation and redness develop

Keep out of reach of children

In case of accidental ingestion, seek medical attention or contact a poison control center immediately.

Directions

- Receive a small amount of foam into palm of hand
- Rub thoroughly over all surfaces of both hands
- Rub hands together until dry

Other information

Store in a cool dry place below 104° F

Inactive ingredients

purified water, dihydroxypropyl PEG-5, linoleammonium chloride, glycereth-2 cocoate, behentrimonium chloride, dihydroxyethyl cocamine oxide

Questions?

Contact Best SanitizersMon-Fri 9am-4pm PST at 888-225-3267

PACKAGE LABEL

NDC 59900-118-06

NDC 59900-118-12

NDC 59900-118-48

Smart San™ alcohol-free hand sanitizer foam